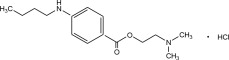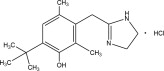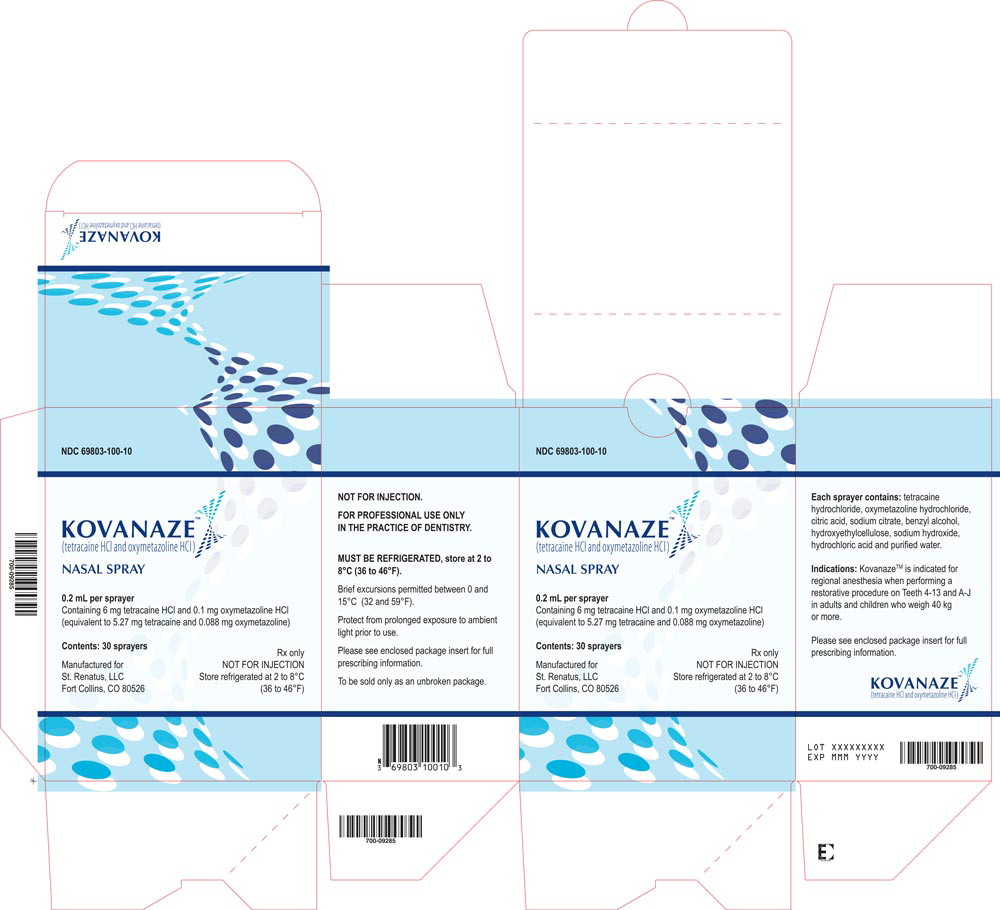 DRUG LABEL: Kovanaze
NDC: 69803-100 | Form: SPRAY
Manufacturer: St. Renatus
Category: prescription | Type: HUMAN PRESCRIPTION DRUG LABEL
Date: 20181116

ACTIVE INGREDIENTS: TETRACAINE HYDROCHLORIDE 30 mg/1 mL; OXYMETAZOLINE HYDROCHLORIDE 0.5 mg/1 mL
INACTIVE INGREDIENTS: BENZYL ALCOHOL; SODIUM HYDROXIDE; HYDROXYETHYL CELLULOSE (2000 MPA.S AT 1%); SODIUM CITRATE; HYDROCHLORIC ACID; ANHYDROUS CITRIC ACID; WATER

HIGHLIGHTS OF PRESCRIBING INFORMATION

These highlights do not include all the information needed to use KOVANAZETM NASAL SPRAY safely and effectively. See full prescribing information for KOVANAZE NASAL SPRAY.
KOVANAZE (tetracaine HCl and oxymetazoline HCl) Nasal Spray
Initial U.S. Approval: 2016

RECENT MAJOR CHANGES

Warnings and Precautions, Methemoglobinemia (5.1) 11/2018

1 INDICATIONS AND USAGE

KOVANAZE contains tetracaine HCl, an ester local anesthetic, and oxymetazoline HCl, a vasoconstrictor. KOVANAZE is indicated for regional anesthesia when performing a restorative procedure on Teeth 4-13 and A-J in adults and children who weigh 40 kg or more (1).

2 DOSAGE AND ADMINISTRATION

KOVANAZE is for intranasal use only (2). Administer KOVANAZE ipsilateral (on the same side) to the maxillary tooth on which the dental procedure will be performed.

Age Group | Dose
Adults (≥ 18 years old) | 2 sprays (0.2 mL per spray), 4 to 5 minutes apart
Adults (≥ 18 years old) | 1 additional spray (0.2 mL) if adequate anesthesia has not been achieved 10 minutes after the second spray
Children who weigh 40 kg or more | 2 sprays (0.2 mL per spray), 4 to 5 minutes apart

3 DOSAGE FORMS AND STRENGTHS

Nasal spray in pre-filled, single-dose sprayer: 6 mg tetracaine HCl and 0.1 mg oxymetazoline HCl (equivalent to 5.27 mg tetracaine and 0.088 mg oxymetazoline) in each 0.2 mL spray (3).

4 CONTRAINDICATIONS

Known hypersensitivity to tetracaine, benzyl alcohol, other ester local anesthetics, p-aminobenzoic acid (PABA), oxymetazoline, or any other component of the product (4).

5 WARNINGS AND PRECAUTIONS

Methemoglobinemia: Cases of methemoglobinemia have been reported in association with local anesthetic use (5.1)

Hypertension and Thyroid Disease: Shown to increase blood pressure in some clinical trial patients. Monitor blood pressure. Use in patients with inadequately controlled hypertension or active thyroid disease is not advised (5.2).

Epistaxis: Use is not recommended in patients with a history of frequent nose bleeds (≥5 per month). If a decision to use is made, monitor these patients carefully (5.3).

Dysphagia: Carefully monitor patients for dysphagia (5.4).

Anaphylactic Reactions: Seek emergency help if an anaphylactic reaction occurs (5.5).

6 ADVERSE REACTIONS

The most common adverse reactions occurring in >10% of patients include rhinorrhea, nasal congestion, nasal discomfort, oropharyngeal pain, and lacrimation increased (6).

Transient, asymptomatic elevations in systolic blood pressure (≥ 25 mm Hg from baseline) and diastolic blood pressures (≥ 15 mm Hg from baseline) have been reported (6).

To report SUSPECTED ADVERSE REACTIONS, contact St. Renatus, LLC at 800-865-4925 or FDA at 1-800-FDA-1088 or www.fda.gov/medwatch.

7 DRUG INTERACTIONS

Monoamine oxidase inhibitors (MAOIs): Concomitant use of MAOIs, nonselective beta adrenergic antagonists, or tricyclic antidepressants may cause hypertension and is not recommended (7.2).

Oxymetazoline-containing products: Discontinue use 24 hours prior to KOVANAZE administration (7.3).

Intranasal products: Avoid concomitant use (7.4).

FULL PRESCRIBING INFORMATION

1 INDICATIONS AND USAGE

KOVANAZETM is indicated for regional anesthesia when performing a restorative procedure on Teeth 4-13 and A-J in adults and children who weigh 40 kg or more.

2 DOSAGE AND ADMINISTRATION

2.1 Important Dosage and Administration Instructions

- KOVANAZE is for intranasal use only.
- Administer ipsilateral (same side) to the maxillary tooth on which the dental procedure will be performed.
- Wait 10 minutes after administration of KOVANAZE to perform a test drill to confirm that the tooth involved is anesthetized. A patient may not experience the same sensations of numbness or tingling of the lips and cheeks associated with injectable dental anesthetics.

2.2 Dosing in Adults (≥ 18 years old)

- 2 sprays (0.2 mL each) administered 4 to 5 minutes apart in the nostril ipsilateral to the maxillary tooth on which the dental procedure will be performed. Initiate the dental procedure 10 minutes after the second spray.
- 1 additional spray (0.2 mL) if adequate anesthesia to initiate the dental procedure has not been achieved 10 minutes after the second spray.

2.3 Dosing in Children (who weigh 40 kg or more)

- 2 sprays (0.2 mL each) administered 4 to 5 minutes apart in the nostril ipsilateral to the maxillary tooth on which the dental procedure will be performed. Initiate the dental procedure 10 minutes after the second spray.

Age Group | Dose
Adults (≥ 18 years old) | - 2 sprays (0.2 mL per spray), 4 to 5 minutes apart - 1 additional spray (0.2 mL) if adequate anesthesia has not been achieved 10 minutes after the second spray
Children who weigh 40 kg or more | - 2 sprays (0.2 mL per spray), 4 to 5 minutes apart

3 DOSAGE FORMS AND STRENGTHS

Nasal spray in pre-filled, single-dose sprayer: 6 mg tetracaine HCl and 0.1 mg oxymetazoline HCl (equivalent to 5.27 mg tetracaine and 0.088 mg oxymetazoline) in each 0.2 mL spray.

4 CONTRAINDICATIONS

KOVANAZE is contraindicated in patients with a history of allergy to or intolerance of tetracaine, benzyl alcohol, other ester local anesthetics, p-aminobenzoic acid (PABA), oxymetazoline, or any other component of the product [see Warnings and Precautions (5.5)] .

5 WARNINGS AND PRECAUTIONS

5.1 Methemoglobinemia

Cases of methemoglobinemia have been reported in association with local anesthetic use. Although all patients are at risk for methemoglobinemia, patients with glucose-6-phosphate dehydrogenase deficiency, congenital or idiopathic methemoglobinemia, cardiac or pulmonary compromise, infants under 6 months of age, and concurrent exposure to oxidizing agents or their metabolites are more susceptible to developing clinical manifestations of the condition. If local anesthetics must be used in these patients, close monitoring for symptoms and signs of methemoglobinemia is recommended.

Signs of methemoglobinemia may occur immediately or may be delayed some hours after exposure, and are characterized by a cyanotic skin discoloration and/or abnormal coloration of the blood. Methemoglobin levels may continue to rise; therefore, immediate treatment is required to avert more serious central nervous system and cardiovascular adverse effects, including seizures, coma, arrhythmias, and death. Discontinue KOVANAZE and any other oxidizing agents. Depending on the severity of the signs and symptoms, patients may respond to supportive care, i.e., oxygen therapy, hydration. A more severe clinical presentation may require treatment with methylene blue, exchange transfusion, or hyperbaric oxygen.

5.2 Risk of Hypertension

KOVANAZE has not been studied in Phase 3 trials in adult dental patients with blood pressure greater than 150/100 or in those with inadequately controlled active thyroid disease. KOVANAZE has been shown to increase blood pressure in some patients in clinical trials. Monitor patients for increased blood pressure. Use in patients with uncontrolled hypertension or inadequately controlled active thyroid disease of any type is not advised [see Adverse Reactions (6.1)] .

5.3 Epistaxis

In clinical trials, epistaxis occurred more frequently with KOVANAZE than placebo. Either do not use KOVANAZE in patients with a history of frequent nose bleeds (≥ 5 per month) or monitor patients with frequent nose bleeds more carefully if KOVANAZE is used. [see Adverse Reactions (6.1)].

5.4 Dysphagia

In clinical trials, dysphagia occurred more frequently with KOVANAZE than placebo. Carefully monitor patients for this adverse reaction.

5.5 Anaphylactic Reactions

Allergic or anaphylactic reactions have been associated with tetracaine, and may occur with other components of KOVANAZE. They are characterized by urticaria, angioedema, bronchospasm, and shock. If an allergic reaction occurs, seek emergency help immediately.

6 ADVERSE REACTIONS

The following adverse reactions are described elsewhere in the labeling:

- Methemoglobinemia [see Warnings and Precautions (5.1)]
- Hypertension [see Warnings and Precautions (5.2)]
- Epistaxis [see Warnings and Precautions (5.3)]
- Dysphagia [see Warnings and Precautions (5.4)]
- Anaphylatic Reactions [see Warnings and Precautions (5.5)]

6.1 Clinical Trials Experience

Because clinical trials are conducted under widely varying conditions, adverse reaction rates observed in the clinical trials of a drug cannot be compared to rates in the clinical trials of another drug and may not reflect the rates observed in clinical practice.

The adverse reactions information described below is from Phase 3 randomized, controlled clinical trials [see Clinical Studies (14)] . These data reflect exposure to KOVANAZE in 154 adult dental patients and 20 pediatric dental patients (aged 7 to 17 years) with a need for an operative restorative dental procedure requiring local anesthesia for a single vital maxillary tooth (other than a maxillary first, second, or third molar) with no evidence of pulpal pathology. [see Clinical Studies (14)].

Common Adverse Reactions in Adult Dental Patients and Pediatric Patients Weighing 40 kg or More

The most common adverse reactions to occur in Phase 3 trials with KOVANAZE in adult dental patients and pediatric dental patients weighing 40 kg or more were rhinorrhea, nasal congestion, nasal discomfort, oropharyngeal pain, and lacrimation increased [ Table 1] .

No serious adverse events with KOVANAZE have occurred [see Clinical Studies (14.1)] .

Table 1: Common Adverse Reactions in ≥ 2% of Phase 3 Adult Dental Patients and Pediatric Patients Weighing 40 kg or More
SOC / Preferred Term | KOVANAZE (N=174) | Active Comparator* (N=54) | Placebo (N=88)
Respiratory System Disorders | 141 (81%) | 50 (93%) | 18 (21%)
Rhinorrhea (runny nose) | 91 (52%) | 20 (37%) | 3 (3%)
Nasal congestion | 56 (32%) | 34 (63%) | 6 (7%)
Nasal discomfort | 45 (26%) | 7 (13%) | 5 (6%)
Oropharyngeal pain (sore throat) | 25 (14%) | 5 (9%) | 0 (0%)
Intranasal hypoesthesia | 18 (10%) | 8 (15%) | 5 (6%)
Pharyngeal hypoesthesia (numb throat) | 17 (10%) | 10 (19%) | 0 (0%)
Throat Irritation | 15 (9%) | 1 (2%) | 0 (0%)
Rhinalgia | 10 (6%) | 3 (6%) | 2 (2%)
Sneezing | 7 (4%) | 2 (4%) | 1 (1%)
Epistaxis | 4 (2%) | 2 (4%) | 0 (0%)
Nasal Dryness | 4 (2%) | 0 (0%) | 1 (1%)
Nervous System Disorders | 39 (22%) | 5 (9%) | 6 (7%)
Headache | 18 (10%) | 3 (6%) | 4 (5%)
Dysgeusia | 14 (8%) | 1 (2%) | 1 (1%)
Sinus headache | 5 (3%) | 0 (0%) | 0 (0%)
Dizziness | 5 (3%) | 0 (0%) | 1 (1%)
Sensory Disturbance | 4 (2%) | 0 (0%) | 0 (0%)
Eye Disorders | 29 (17%) | 8 (15%) | 4 (5%)
Lacrimation increased (watery eye) | 23 (13%) | 6 (11%) | 4 (5%)
Gastrointestinal Disorders | 16 (9%) | 5 (9%) | 3 (3%)
Oral Discomfort | 4 (2%) | 0 (0%) | 0 (0%)
Investigations | 12 (7%) | 0 (0%) | 4 (5%)
BP systolic increased | 8 (5%) | 0 (0%) | 2 (2%)
BP diastolic increased | 6 (3%) | 0 (0%) | 1 (1%)
Cardiac Disorders | 8 (5%) | 5 (9%) | 1 (1%)
Bradycardia | 5 (3%) | 3 (6%) | 1 (1%)
Vascular Disorders | 6 (3%) | 2 (4%) | 1 (1%)
Hypertension | 5 (3%) | 1 (2%) | 1 (1%)
* Active Comparator was tetracaine only spray used in two clinical studies in adults.

Intranasal ulcerations, some of which were transient, were noted to have occurred following treatment with KOVANAZE. In Phase 3 trials, 6 (3%) patients who received KOVANAZE, but no patients who received placebo, developed nasal ulcers that were present on exam the same day as KOVANAZE dosing. Three (2%) KOVANAZE and 2 (2%) placebo-treated patients without nasal ulcerations on the day of KOVANAZE or placebo dosing were observed to have nasal ulcerations at the next day follow-up visit.

Less Common Adverse Reactions in Phase 3 Clinical Trials Adult Dental Patients and Pediatric Dental Patients Weighing 40 kg or More

Dysphagia (i.e., the sensation of difficult swallowing) is a notable adverse reaction reported in Phase 3 trials, occurring in 1.15% of patients.

For medical advice about adverse reactions, contact your medical professional. To report SUSPECTED ADVERSE REACTIONS, contact St. Renatus, LLC at 800-865-4925 or FDA at 1-800-FDA-1088 or www.fda.gov/medwatch/.

7 DRUG INTERACTIONS

7.1 Drugs That May Cause Methemoglobinemia When Used with KOVANAZE

Patients who are administered local anesthetics may be at increased risk of developing methemoglobinemia when concurrently exposed to the following drugs, which could include other local anesthetics:

Examples of Drugs Associated with Methemoglobinemia:

Class | Examples
Nitrates/Nitrites | nitric oxide, nitroglycerin, nitroprusside, nitrous oxide
Local anesthetics | articaine, benzocaine, bupivacaine, lidocaine, mepivacaine, prilocaine, procaine, ropivacaine, tetracaine
Antineoplastic agents | cyclophosphamide, flutamide, hydroxyurea, ifosfamide, rasburicase
Antibiotics | dapsone, nitrofurantoin, para-aminosalicylic acid, sulfonamides
Antimalarials | chloroquine, primaquine
Anticonvulsants | phenobarbital, phenytoin, sodium valproate,
Other drugs | acetaminophen, metoclopramide, quinine, sulfasalazine

7.2 Monoamine Oxidase Inhibitors

Use of KOVANAZE in combination with monoamine oxidase inhibitors (MAOIs), nonselective beta adrenergic antagonists, or tricyclic antidepressants may cause hypertension and is not recommended. Alternative anesthetic agents should be chosen for patients who cannot discontinue use of MAOIs, nonselective beta adrenergic antagonists, or tricyclic antidepressants.

7.3 Oxymetazoline-containing Products

Concomitant use with other oxymetazoline-containing products (such as Afrin®) has not been adequately studied. Use of KOVANAZE with other products containing oxymetazoline may increase risk of hypertension, bradycardia, and other adverse events associated with oxymetazoline. Discontinue use 24 hours prior to administration of KOVANAZE.

7.4 Intranasal Products

Oxymetazoline has been known to slow the rate, but not affect the extent of absorption of concomitantly administered intranasal products. Do not administer other intranasal products with KOVANAZE.

8 USE IN SPECIFIC POPULATIONS

8.1 Pregnancy

Risk Summary

Limited published data on tetracaine use in pregnant women are not sufficient to inform any risks. Published epidemiologic studies of nasal oxymetazoline used as a decongestant during pregnancy do not identify a consistent association with any specific malformation or pattern of malformations [see Data] . In animal reproduction and development studies, oxymetazoline given subcutaneously to rats during the period of organogenesis caused structural abnormalities at a dose approximately 7.6 times the exposure of oxymetazoline HCl at the 0.3 mg maximum recommended human dose (MRHD) of KOVANAZE. In a pre- and post-natal development study, oxymetazoline given subcutaneously to rats caused embryo-fetal toxicity manifested by reduced implantation sites and live litter sizes at approximately 1.5 times the MRHD and increased pup mortality at 6 times the MRHD. No adverse developmental effects were observed following subcutaneous administration of tetracaine HCl only to rats and rabbits during organogenesis at 32 and 6 times, respectively, the estimated exposure of tetracaine HCl at the 18 mg MRHD of KOVANAZE [see Data] .

In the U.S. general population, the estimated background risk of major birth defects and miscarriage in clinically recognized pregnancies is 2 to 4% and 15 and to 20%, respectively.

Data

Human Data

Published epidemiologic studies of nasal oxymetazoline used as a decongestant during pregnancy do not identify a consistent association with any specific malformation or pattern of malformations. These data are limited by the small number of cases exposed, multiple comparisons which may have resulted in chance findings, and analyses based on decongestants as a group.

Animal Data

In an embryo-fetal development study, pregnant rats were administered subcutaneous doses of oxymetazoline HCl only at 0.1 mg/kg, tetracaine HCl only at 7.5 mg/kg, or oxymetazoline HCl at 0.01, 0.03, and 0.1 mg/kg/day in combination with 7.5 mg/kg tetracaine HCl during the period of organogenesis (Gestational Days [GD] 7-17). Oxymetazoline HCl treatment at 0.1 mg/kg/day (7.6 times the oxymetazoline AUC exposure at the maximum recommended human dose [MRHD] of KOVANAZE [3 mg oxymetazoline HCl and 18 mg tetracaine HCl]) caused reduced fetal weight and structural abnormalities including external and skeletal malformations (e.g., short forelimb digits, fused arches in thoracic vertebrae, fused ribs, and irregular number of ribs), and variations (e.g., irregularly shaped arches and increased bifid centra in thoracic vertebrae, and un-ossified forelimb phalanx) in the presence of maternal toxicity (reduced food consumption, body weight gain, and absolute body weight); however, the structural abnormality findings cannot be clearly attributed to the maternal toxicity. Adverse developmental effects were not observed when pregnant rats were co-administered the same dose of oxymetazoline HCl in combination with 7.5 mg/kg/day tetracaine HCl, or with 7.5 mg/kg/day tetracaine HCl alone. The no-observed-adverse-effect-level (NOAEL) for fetal effects was 0.03 mg/kg/day oxymetazoline HCl (1.5 times the oxymetazoline AUC exposure at the MRHD) and 7.5 mg/kg/day tetracaine HCl (30 times the AUC exposure as measured by PBBA [major tetracaine metabolite] at the MRHD).

In other embryo-fetal development studies, tetracaine base alone administered subcutaneously did not cause structural abnormalities in rats at doses up to 10 mg/kg/day (approximately 6.1 times the MRHD level of 18 mg tetracaine HCl by body surface area (BSA) comparison) or in rabbits at subcutaneous doses up to 5 mg/kg/day (approximately 6.1 times the MRHD level by BSA comparison).

In a prenatal and postnatal development study, pregnant rats were given subcutaneous doses of oxymetazoline HCl only at 0.1 mg/kg/day, tetracaine HCl only at 7.5 mg/kg/day, and oxymetazoline HCl at 0.01, 0.03, and 0.1 mg/kg/day in combination with 7.5 mg/kg/day tetracaine HCl from GD 7 to Lactation Day [LD] 20 (corresponding to the beginning of organogenesis through parturition and subsequent pup weaning). Oxymetazoline HCl treatment decreased the mean number of implant sites/litter at ≥ 0.03 mg/kg (≥ 1.5 times the oxymetazoline AUC exposure at the MRHD) when administered with 7.5 mg/kg tetracaine HCl (approximately 9%) and without tetracaine HCl (5.5%), which resulted in a reduction in live litter sizes in these groups. At the end of the lactation period, fetal body weights were significantly decreased at 0.1 mg/kg oxymetazoline HCl (6 times the oxymetazoline AUC exposure at the MRHD) when administered alone (19%) and co-administered with 7.5 mg/kg/day tetracaine HCl (11%). In addition, a decrease in pup survival was observed at the 0.1/7.5 mg/kg oxymetazoline HCl/tetracaine HCl dose (91.9%) compared to the control (99.6%), but no effects in any other groups. Maternal toxicity (e.g., mortality and reduced body weight gain, absolute body weight and food consumption) occurred in groups administered 0.1 mg/kg/day oxymetazoline HCl; however, the adverse developmental findings observed at this dose cannot clearly be attributed to the maternal toxicity. There were no adverse effects on sexual maturation, neurobehavioral, or reproductive function in the offspring at any maternal dose. The no-effect level for oxymetazoline HCl for maternal reproduction was 0.01 mg/kg/day (0.5 times oxymetazoline AUC exposure at the MRHD) and for pup growth and development was 0.03 mg/kg/day (1.5 times oxymetazoline AUC exposure at the MRHD). The no-effect level for tetracaine HCl for maternal reproduction and pup growth and development was 7.5 mg/kg/day (12 times the AUC exposure as measured by PBBA at the MRHD).

8.2 Lactation

Risk Summary

There are no data on the presence of tetracaine, oxymetazoline, or their metabolites in human milk, the effects on the breastfed infant, or the effects on milk production. Detectable levels of oxymetazoline, tetracaine and the major metabolite of tetracaine, p-butylaminobenzoic acid (PBBA), were found in the milk of lactating rats following subcutaneous administration of oxymetazoline HCl in combination with tetracaine HCl during the period of organogenesis through parturition and subsequent pup weaning [see Data] . Due to species-specific differences in lactation physiology, animal data may not reliably predict drug levels in human milk.

The developmental and health benefits of breastfeeding should be considered along with the mother's clinical need for KOVANAZE and any potential adverse effects on the breastfed infant from KOVANAZE or from the underlying maternal condition.

Data

In a pre- and post-natal development study, rats were given oxymetazoline HCl subcutaneously at doses of 0.01, 0.03, and 0.1 mg/kg/day (0.6, 1.5, and 7.6 times, respectively, the oxymetazoline AUC exposure at the MRHD) in combination with 7.5 mg/kg tetracaine HCl (12 times the AUC exposure as measured by PBBA at the MRHD) from Gestational Day [GD] 7 to Lactation Day [LD] 20. Concentrations of oxymetazoline, tetracaine, and PBBA were measured in the milk of lactating rats at approximately 2 hours postdose on LD 15. The concentrations of oxymetazoline were generally dose dependent (2.5, 7.0, and 33.8 ng/mL at 0.01, 0.03, and 0.1 mg/kg/day, respectively). The concentrations of tetracaine and PBBA were generally similar across all 7.5 mg/kg/day tetracaine HCl dosing groups regardless of the presence of oxymetazoline (54.2 – 72.9 ng/mL for tetracaine, and 100.5 – 131.2 ng/mL for PBBA).

8.3 Females and Males of Reproductive Potential

Infertility

No information is available on fertility effects in humans.

Females

Based on animal data, KOVANAZE may reduce fertility in females of reproductive potential. In female rats, decreased fertility noted as a decrease in litter size occurred at 0.7 times the oxymetazoline AUC exposure at the MRHD of KOVANAZE. It is not known if the effects on fertility are reversible [ see Nonclinical Toxicology (13.1)] .

Males

Based on animal data, KOVANAZE may reduce male fertility. In male rats, decreased sperm motility and sperm concentration occurred at approximately 2 times the oxymetazoline AUC exposure at the MRHD of KOVANAZE [see Nonclinical Toxicology (13.1)] .

8.4 Pediatric Use

KOVANAZE has not been studied in pediatric patients under 3 years of age and is not advised for use in pediatric patients weighing less than 40 kg because efficacy has not been demonstrated in these patients [see Clinical Studies (14.2)] .

8.5 Geriatric Use

Clinical studies of KOVANAZE did not include sufficient numbers of patients aged 65 and over to determine whether they respond differently from younger patients. Other reported clinical experience has not identified differences in responses between the elderly and younger patients. Monitor geriatric patients for signs of local anesthetic toxicity, reflecting the greater frequency of decreased hepatic, renal, or cardiac function, and of concomitant disease or other drug therapy.

Of note, comparisons of KOVANAZE safety and efficacy results were generally similar among dental patients who were > 50 years old (n=66) and ≤ 50 years old (n=148). However, a trend toward a higher incidence of notable increases in systolic blood pressure was observed in dental patients > 50 years of age compared with patients ≤ 50 years of age (16.6% vs 1.4, respectively) [see Adverse Reactions (6.1)]. These increases in blood pressure measurements were generally asymptomatic and transient in nature, and all spontaneously resolved without the need for medical intervention [see Clinical Studies (14.1)] .

8.6 Hepatic Disease

Because of an inability to metabolize local anesthetics, those patients with severe hepatic disease may be at a greater risk of developing toxic plasma concentrations of tetracaine. Monitor patients with hepatic disease for signs of local anesthetic toxicity.

8.7 Pseudocholinesterase Deficiency

Because of an inability to metabolize local anesthetics, those patients with pseudocholinesterase deficiency may be at a greater risk of developing toxic plasma concentrations of tetracaine. Monitor patients with pseudocholinesterase deficiency for signs of local anesthetic toxicity.

10 OVERDOSAGE

No addictive properties have been reported in the literature for either tetracaine or oxymetazoline, but there have been numerous case reports of unintended overdose for both compounds. Side effects in adults and children associated with oxymetazoline overdose include dizziness, chest pain, headaches, myocardial infarction, stroke, visual disturbances, arrhythmia, hypertension, or hypotension. Side effects of tetracaine overdose include rapid circulatory collapse, cardiac arrest, and cerebral events.

Possible rebound nasal congestion, irritation of nasal mucosa, and adverse systemic effects (particularly in children), including serious cardiac events, have been associated with overdosage and/or prolonged or too frequent intranasal use of oxymetazoline containing agents.

Accidental ingestion of imidazoline derivatives (i.e., oxymetazoline, naphazoline, tetrahydrozoline) in children has resulted in serious adverse events requiring hospitalization (e.g., coma, bradycardia, decreased respiration, sedation, and somnolence).

Patients should be instructed to avoid using oxymetazoline-containing products (such as Afrin®) and other α-adrenergic agonists within 24 hours prior to their scheduled dental procedure [see Drug Interactions (7.3)] .

Management of an overdose includes close monitoring, supportive care, and symptomatic treatment.

11 DESCRIPTION

KOVANAZE (tetracaine HCl and oxymetazoline HCl) Nasal Spray is a clear aqueous solution in a pre-filled, single-dose intranasal sprayer. The solution pH is 6.0 ± 1.0. The product contains two active ingredients: 30 mg/mL tetracaine HCl (equivalent to 26.4 mg/mL tetracaine) and 0.5 mg/mL oxymetazoline hydrochloride (equivalent to 0.44 mg/mL oxymetazoline). Each spray delivers 0.2 mL of solution containing 6 mg tetracaine hydrochloride (equivalent to 5.27 mg tetracaine) and 0.1 mg of oxymetazoline hydrochloride (equivalent to 0.088 mg oxymetazoline). The product also contains citric acid, sodium citrate, hydroxyethylcellulose, benzyl alcohol, and water. Sodium hydroxide and/or hydrochloric acid are added for pH adjustment as needed.

Tetracaine hydrochloride is an ester local anesthetic. Chemically it is 2-(dimethylamino)ethyl 4-(butylamino)benzoate hydrochloride. Its molecular weight is 300.8 for the hydrochloride salt and 264.4 for the free base. It is freely soluble in water and soluble in ethanol. Its structural formula is:

Oxymetazoline hydrochloride is a vasoconstrictor. Chemically it is 3-[(4,5-dihydro-1 H-imidazol-2-yl)methyl]-6-(1,1,-dimethylethyl)-2,4-dimethylphenol mono-hydrochloride. Its molecular weight is 296.8 for the hydrochloride salt and 260.4 for the free base. It is freely soluble in water and ethanol and has a partition coefficient of 0.1 in octanol/water. Its structural formula is:

12 CLINICAL PHARMACOLOGY

12.1 Mechanism of Action

Tetracaine is a local anesthetic of the ester type and exerts its activity by blocking sodium ion channels required for the initiation and conduction of neuronal impulses. Oxymetazoline is an imidazoline derivative with sympathomimetic activity. It is believed to be a mixed α1/α2-adrenoceptor agonist and, by stimulating adrenergic receptors, it elicits vasoconstriction of dilated arterioles and reduces nasal blood flow.

12.3 Pharmacokinetics

Absorption

Following nasal administration of 0.6 mL KOVANAZE in adult subjects (n=24), oxymetazoline attained maximum concentrations within approximately 10 minutes following the end of dosing. The observed mean oxymetazoline Cmax and AUC0-inf value were 1.78 ng/mL and 4.24 ng.h/mL, respectively. The observed median Tmax was 5 minutes.

Plasma concentrations of tetracaine in all subjects were at or below the limit of assay quantification (0.05 ng/mL). Of all plasma samples analyzed, only one quantifiable tetracaine concentration was observed in a single sample from one subject, which was at the limit of assay quantification. The primary metabolite of tetracaine, p-butylaminobenzoic acid (PBBA) achieved peak concentrations within approximately 25 minutes following the end of KOVANAZE dosing. The observed mean PBBA Cmax and AUC0-inf value were 465 ng/mL and 973 ng.h/mL, respectively. The observed median Tmax was 20 minutes.

Distribution

Protein binding and distribution of oxymetazoline and PBBA have not been determined. Plasma protein binding of tetracaine has been reported to be 75% to 85%.

Elimination

The terminal half-life of oxymetazoline in plasma following nasal administration of KOVANAZE to adult subjects is approximately 5.2 hours.

The elimination half-life and apparent clearance of tetracaine could not be determined after KOVANAZE administration because it is rapidly and thoroughly hydrolyzed in plasma. The plasma half-life of PBBA is approximately 2.6 hours in adult subjects.

Metabolism

Oxymetazoline is converted to a glucuronide conjugate in vitro by UGT1A9.

Tetracaine is rapidly and thoroughly cleaved by esterases in plasma and other tissues to PBBA and dimethylaminoethanol. These metabolites have an unspecified activity.

Excretion

The apparent clearance of oxymetazoline after nasal administration of KOVANAZE has not been determined. It is thought that the primary route of oxymetazoline elimination at clinically relevant concentrations is by renal excretion.

PBBA clearance cannot be determined after administration of tetracaine.

Special Populations

Pediatrics:

In subjects 4-15 years of age (n=18) that received KOVANAZE doses of 0.1 mL (10 to < 20 kg body weight), 0.2 mL (20 to < 40 kg), or 0.4 mL (≥ 40 kg), oxymetazoline attained maximum concentrations within approximately 10 minutes to 30 minutes (median time) following the end of dosing. The observed oxymetazoline mean Cmax values were 0.37 ± 0.43, 0.85 ± 0.45, and 1.2 ± 0.39 ng/mL in the 0.1 mL, 0.2 mL, and 0.4 mL dose groups, respectively. The observed oxymetazoline mean AUC0-inf values were 0.99 (AUC can be calculated only in one subject), 2.53 ± 1.08, and 2.64 ± 0.41 ng.h/mL in the 0.1 mL, 0.2 mL, and 0.4 mL dose groups, respectively. Mean elimination half-life values for oxymetazoline were approximately 1.6 to 4.3 hours across pediatric dose groups.

Plasma concentrations of tetracaine were below the limit of assay quantification (0.05 ng/mL) in all subjects.

PBBA attained maximum concentrations within approximately 20 minutes to 30 minutes (median time) following the end of dosing. The observed PBBA mean Cmax values were 166 ± 71, 345 ± 172, and 365 ± 30 ng/mL in the 0.1 mL, 0.2 mL, and 0.4 mL dose groups, respectively. The observed PBBA mean AUC0-inf values were 529 ± 222, 826 ± 606, and 665 ± 86 ng.h/mL in the 0.1 mL, 0.2 mL, and 0.4 mL dose groups, respectively. Mean elimination half-life values for PBBA were approximately 1.6 to 2.8 hours across pediatric dose groups.

Elderly: The pharmacokinetics of KOVANAZE were not evaluated in subjects greater than 50 years of age.

Renal or Hepatic Impairment: The pharmacokinetics of oxymetazoline, tetracaine, and PBBA were not evaluated after nasal administration of KOVANAZE in subjects with renal or hepatic impairment.

Race: There were insufficient data to evaluate the effect of race on oxymetazoline, tetracaine, and PBBA pharmacokinetics after nasal administration of KOVANAZE.

13 NON-CLINICAL TOXICOLOGY

13.1 Carcinogenesis, Mutagenesis, Impairment of Fertility

Carcinogenesis

Long-term studies in animals have not been performed to evaluate the carcinogenic potential of tetracaine or oxymetazoline.

Mutagenesis

Tetracaine base was negative in the in vitro Ames bacterial reverse mutation assay and the in vivo mouse micronucleus assay. In the in vitro chromosome aberration assay using Chinese hamster ovary cells, tetracaine base was negative in the absence of metabolic activation, and equivocal in the presence of metabolic activation. No studies have been conducted to evaluate the mutagenic potential of oxymetazoline.

Impairment of Fertility

Male and female rats were given subcutaneous doses of oxymetazoline HCl alone at 0.1 mg/kg/day, tetracaine HCl alone at 7.5 mg/kg/day, or the combination of oxymetazoline HCl at 0.01, 0.03, or 0.1 mg/kg/day oxymetazoline with 7.5 mg/kg/day tetracaine HCl prior to and during mating. Oxymetazoline HCl at ≥ 0.03 mg/kg/day reduced the percentage of motile sperm and sperm counts at 2 times the oxymetazoline AUC exposure at the MRHD of KOVANAZE. There were no effects on male mating behavior at any dose tested. The no-effect level for sperm effects was 0.01 mg/kg/day (0.7 times the oxymetazoline AUC exposure at the MRHD of KOVANAZE).

In female rats, a reduction in the number of viable embryos was observed at oxymetazoline AUC exposures equivalent to 0.7 times the MRHD and higher, given alone or in combination with tetracaine HCl. Reduced numbers of corpora lutea and implantation sites were observed at 7.5 times the oxymetazoline AUC exposure at the MRHD in animals given oxymetazoline HCl alone or in combination with tetracaine HCl. These effects were attributed to oxymetazoline HCl because similar effects were not observed in rats given tetracaine HCl alone. A no-effect level for fertility in female rats was not established in this study.

No effects on male or female fertility were attributed to tetracaine HCl at 7.5 mg/kg/day (28 and 33 times the AUC exposure for males and females, respectively, as measured by PBBA [major tetracaine metabolite] at the MRHD of KOVANAZE).

14 CLINICAL STUDIES

The efficacy of KOVANAZE Nasal Spray for regional anesthesia when performing a restorative procedure on Teeth 4-13 and A-J has been evaluated in three adult dental patient studies, as well as one pediatric dental patient study. The primary endpoint for all four studies was the successful completion of a restorative operative dental procedure without the need for a rescue injection. One adult dental study was terminated early for reasons related to the administration of KOVANAZE. Unlike the other studies conducted, in this study all three sprays were delivered horizontally.

14.1 Studies in Adults

Study 1

Study 1 was a Phase 3, multicenter, randomized, double-blind, placebo and active-controlled, parallel-groups study designed to compare the efficacy and safety of intranasally administered KOVANAZE to both tetracaine HCl alone and placebo, for providing dental anesthesia sufficient to allow completion of the standard dental procedure on a single maxillary tooth (#4-13) in adults.

A total of 110 patients were enrolled in two clinical centers and randomized to receive three 0.2 mL intranasal sprays of either KOVANAZE (n=44), tetracaine alone (n=44), or placebo (n=22). All randomized patients completed the study dental procedure.

Fifty-three percent (53%) of randomized patients were female and 76% were White, with a mean age of 35 years (range 18 to 73 years).

Eighty-four percent (95% CI: 70%, 93%) of KOVANAZE patients were able to complete the dental procedure without the need for rescue medication compared to 27% (95% CI: 15%, 43%) who received tetracaine alone and 27% (95% CI: 11%, 50%) who received placebo.

KOVANAZE had a lower success rate for dental procedures on the 2nd pre-molar (teeth #4 and #13) compared with more anterior teeth (#5 through #12): 63% for the 2nd pre-molars vs 96% for more anterior teeth.

In this trial, the median duration of a dental procedure successfully completed with KOVANAZE was 11 minutes, although one successfully completed dental procedure was as long as 43 minutes. Of the people that needed rescue medication in the KOVANAZE arm, they required it within the first 6 minutes following the start of the dental procedure.

Study 2

Study 2 was a Phase 3, multicenter, randomized, double-blind, parallel-groups study designed to compare the efficacy and safety of intranasally administered KOVANAZE to placebo, for providing dental anesthesia sufficient to allow completion of the standard dental procedure on a single maxillary tooth (#4-13) in adults.

A total of 150 adult patients were enrolled at three study centers and received either KOVANAZE (n=100) or placebo (n=50) as a dose of two or three 0.2 mL intranasal sprays. All except two randomized patients (one each in the KOVANAZE and placebo groups) completed the study dental procedure.

Fifty-five percent (55%) of randomized patients were female and 63% were White, with a mean age of 41 years (range 18 to 78 years).

Eighty-eight percent (95% CI: 80%, 94%) of KOVANAZE patients were able to complete the dental procedure without the need for rescue medication compared to 28% (95% CI: 16%, 43%) of patients who received placebo.

KOVANAZE had a lower success rate for dental procedures on the 2nd pre-molar (teeth #4 and #13) compared with more anterior teeth (#5 through #12): 64% for the 2nd pre-molars vs 96% for more anterior teeth.

14.2 Study in Children

Study 3

Study 3 was a Phase 3, multicenter, randomized, double-blind, parallel-groups study designed to compare the efficacy and safety of intranasally administered KOVANAZE to placebo for providing dental anesthesia sufficient to allow completion of the standard dental procedure on a single maxillary tooth (permanent teeth 4-13 or primary teeth A-J) for pediatric patients aged 3 through 17.

A total of 90 patients, 3 through 17 years of age inclusive, were enrolled at two study centers. Patients received one or two intranasal sprays of either KOVANAZE (n=60) or placebo (n=30) based on body weight: one 0.1 mL spray for patients weighing 10 kg to less than 20 kg; two 0.1 mL sprays for 20 kg to less than 40 kg; or two 0.2 mL sprays for patients weighing 40 kg or more. All except one randomized patient in the KOVANAZE group completed the study dental procedure.

Fifty-one percent (51%) of randomized patients were male and 89% were White, with a mean age of 8 years (range 3 to 17 years).

Even though a greater percentage of patients were able to complete the dental procedure without the need for rescue anesthesia for KOVANAZE: 77% for KOVANAZE (95% CI: 64%, 87%) compared to 53% for placebo (95% CI: 34%, 72%) an analysis by weight indicated that efficacy was only established for patients weighing 40 kg or more [see Table 3] .

Table 3: Success Rates by Weight Group in the Pediatric Dental Patients (Study 3)
Successful Anesthetic Response by Weight N (%) | KOVANAZE (N = 60) | Placebo (N = 30)
40 kg or more | 18/20 (90%) | 4/10 (40%)
20 to less than 40 kg | 14/24 (58%) | 5/12 (42%)
10 to less than 20 kg | 14/16 (88%) | 7/8 (88%)

16 HOW SUPPLIED/STORAGE AND HANDLING

KOVANAZE Nasal Spray is supplied as pre-filled, single-dose sprayers containing a clear aqueous solution of 30 mg/mL of tetracaine hydrochloride (equivalent to 26.4 mg/mL tetracaine) and 0.5 mg/mL of oxymetazoline hydrochloride (equivalent to 0.44 mg/mL oxymetazoline). Each sprayer delivers 0.2 mL.

The product is available as:

- NDC 69803-100-10: Box of 30 sprayers

Store between 2° and 8°C (36° and 46°F); excursions permitted between 0° and 15°C (32° and 59°F) [see USP controlled cold temperature].

Discard any unused solution. DO NOT use if drug is left out at room temperature for more than 5 days.

17 PATIENT COUNSELING INFORMATION

- Inform patients that use of local anesthetics may cause methemoglobinemia, a serious condition that must be treated promptly. Advise patients or caregivers to seek immediate medical attention if they or someone in their care experience the following signs or symptoms: pale, gray, or blue colored skin (cyanosis); headache; rapid heart rate; shortness of breath; lightheadedness; or fatigue [see Warnings and Precautions (5.1)] .
- Inform patients of the likelihood of expected side effects (including runny nose, nasal congestion, mild nose bleeds, dizziness, and/or a sensation of difficulty in swallowing) that should resolve within the same day. Instruct patients to contact their dentist or health care professional if these symptoms persist [see Adverse Reactions (6)] .
- Advise patients to inform the dental practitioner if they are taking monoamine oxidase inhibitors (MAOIs), nonselective beta adrenergic antagonists, or tricyclic antidepressants [see Drug Interactions (7.2)] .
- Instruct patients to avoid using oxymetazoline-containing products (such as Afrin® and other α-adrenergic agonists) within 24 hours prior to their scheduled dental procedure. [see Drug Interactions (7.3)] .
- Advise patients of the signs and symptoms of hypersensitivity reactions and to seek immediate medical attention should they occur [see Warnings and Precautions (5.5)] .

St. Renatus, LLC
Manufactured for:
St. Renatus, LLC
Fort Collins, CO 80526

KOVANAZE is a trademark of St. Renatus, LLC.

Principal Display Panel - Box Label

NDC 69803-100-10

KOVANAZE
(tetracaine HCl and oxymetazoline HCl)

NASAL SPRAY

0.2 mL per sprayer
Containing 6 mg tetracaine HCl and 0.1 mg oxymetazoline HCl

(equivalent to 5.27 mg tetracaine and 0.088 mg oxymetazoline)

Contents: 30 sprayers

Rx only

NOT FOR INJECTION

Store refrigerated at 2 to 8°C (36 to 46°F)

Manufactured for

St. Renatus, LLC

Fort Collins, CO 80526